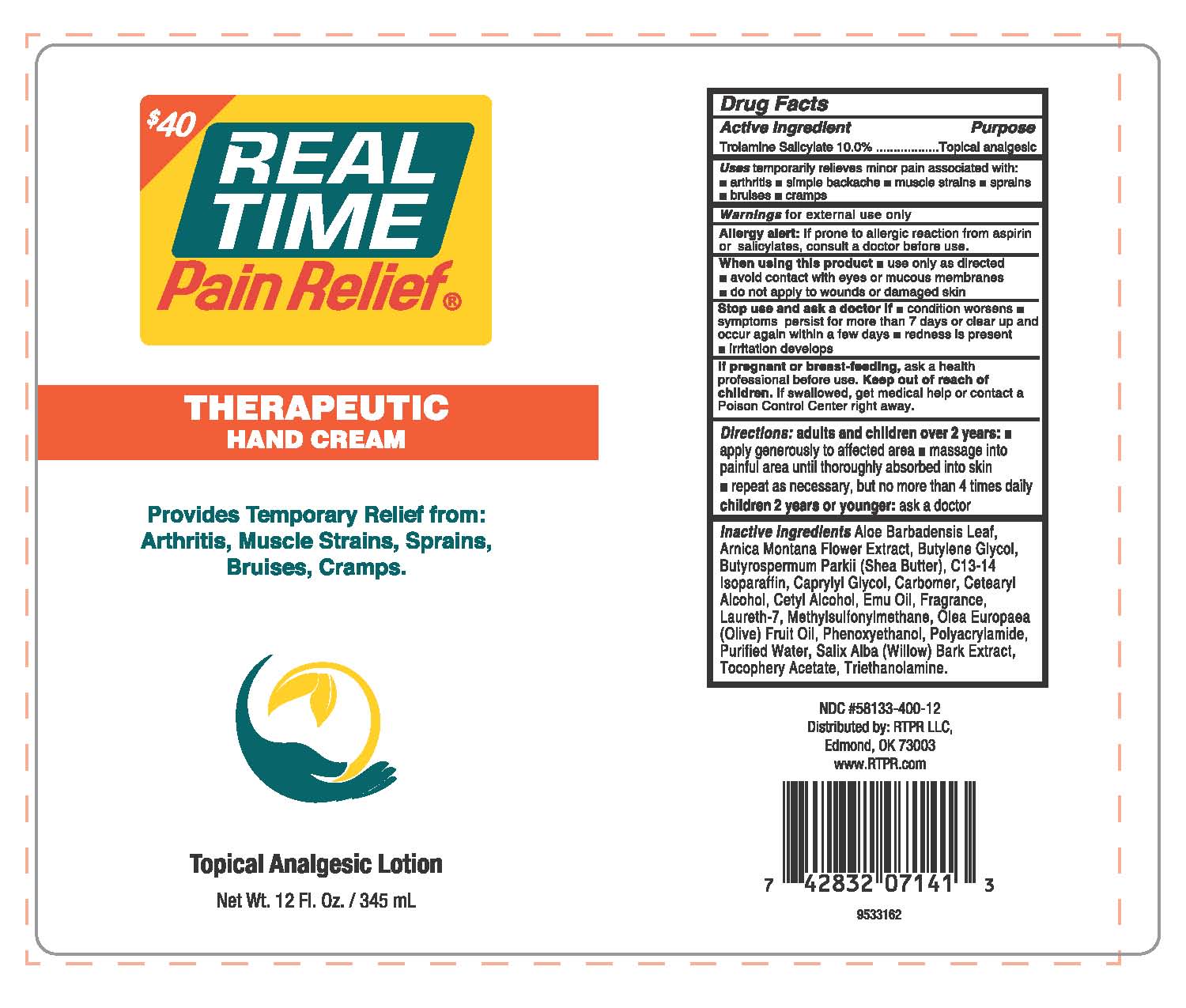 DRUG LABEL: Real Time Pain Relief Therapeutic Hand Cream
NDC: 58133-400 | Form: LOTION
Manufacturer: Cosmetic Specialty Labs, Inc.
Category: otc | Type: HUMAN OTC DRUG LABEL
Date: 20180103

ACTIVE INGREDIENTS: TROLAMINE SALICYLATE 10 g/100 mL
INACTIVE INGREDIENTS: DIMETHYL SULFONE; ARNICA MONTANA FLOWER; BUTYLENE GLYCOL; .ALPHA.-TOCOPHEROL ACETATE; CETOSTEARYL ALCOHOL; EMU OIL; LAURETH-7; BUTYROSPERMOL; C13-14 ISOPARAFFIN; CAPRYLYL GLYCOL; CARBOMER 940; ALOE VERA LEAF; CETYL ALCOHOL; PROPYLPARABEN; TROLAMINE; WATER; OLEA EUROPAEA FRUIT VOLATILE OIL; 2-(2-(2-(2-PHENOXYETHOXY)ETHOXY)ETHOXY)ETHANOL; POLYACRYLAMIDE (10000 MW); SALIX ALBA BARK

Real Time Pain Relief Therapeutic Hand Cream

Active ingredient Purpose

Trolamine Salicylate - 10% Topical Analgesic

Purpose

Topical Analgesic

Uses

Uses: temporarily relieves minor pain associated with • arthritis • simple backache •muscle strains • bruises • cramps

Warnings For external use only

Allergy alert: if prone to allergic reaction from aspirin or salicylates, consult a doctor before use.

When using this product • use only as directed • avoid contact with eyes or muscous membranes • do not apply to wounds or damaged skin

Stop use and ask a doctor if • condition worsens • symptoms persist for more than 7 days or clear up and occur again within a few days • redness is present • irritation develops

If pregnant or breast-feeding, ask a health professional before use.

KEEP OUT OF REACH OF CHILDREN

Keep out of reach of the children. If product is swallowed, get medical help or contact a Poison Control Center right away

Directions

adults and children over 2 years:

- apply generously to affected area
- massage into painful area until thoroughly absorbed into skin
- repeat as necessary, but no more than 4 times daily

children 2 years or younger: ask a doctor

Inactive ingredients:

Aloe Barbadensis Leaf, Arnica Montana Flower Extract, Butylene Glycol, Butyrospermum Parkii (Shea Butter), C13-14 Isoparaffin, Caprylyl Glycol, Carbomer, Cetearyl Alcohol, Cetyl Alcohol, Emu Oil, Fragrance, Laureth-7, Methylsulfonylmethane, Olea Europaea (Olive) Fruit Oil, Phenoxyethanol, Polyacrylamide, Purified Water, Salix Alba (Willow) Bark Extract, Tocopheryl Acetate, Triethanolamine.